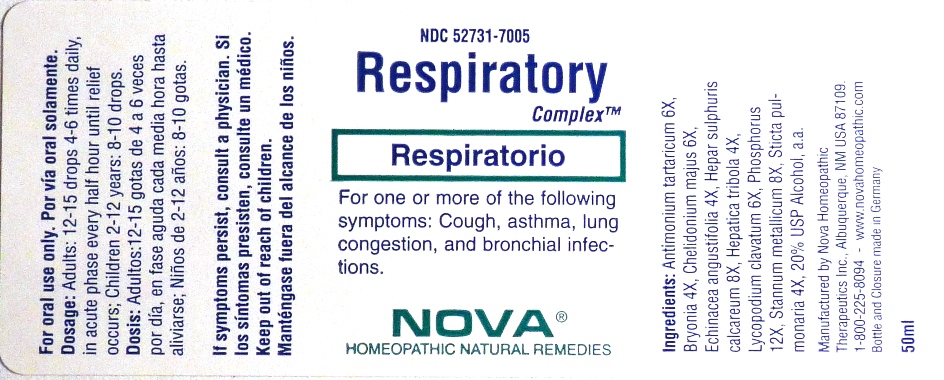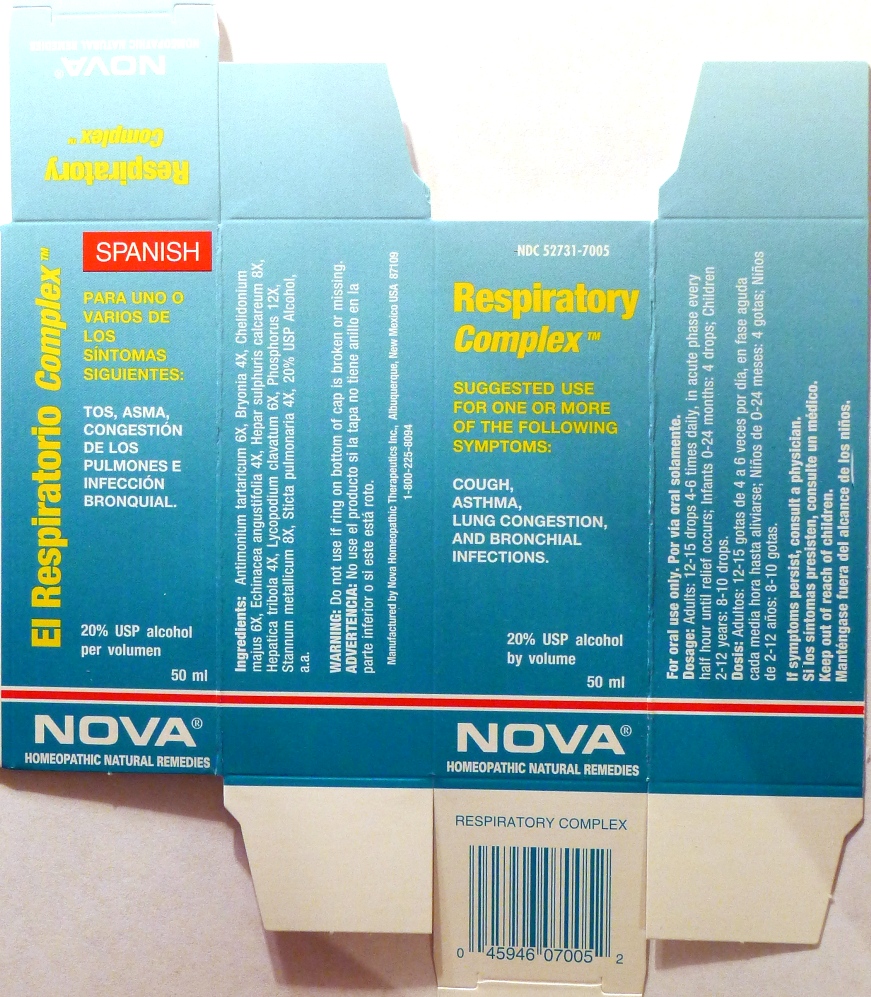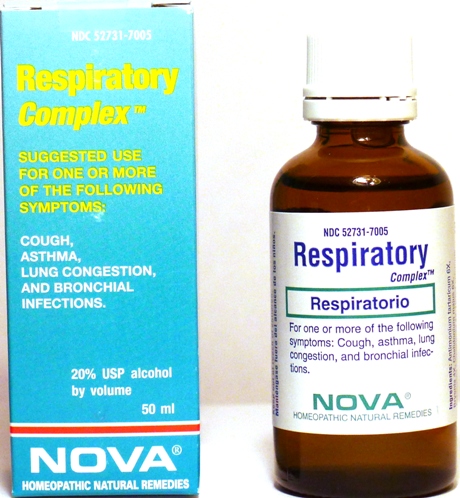 DRUG LABEL: Respiratory Complex
NDC: 52731-7005 | Form: LIQUID
Manufacturer: Nova Homeopathic Therapeutics, Inc.
Category: homeopathic | Type: HUMAN OTC DRUG LABEL
Date: 20110601

ACTIVE INGREDIENTS: ANTIMONY POTASSIUM TARTRATE 6 [hp_X]/1 mL; BRYONIA ALBA ROOT 4 [hp_X]/1 mL; CHELIDONIUM MAJUS 6 [hp_X]/1 mL; ECHINACEA ANGUSTIFOLIA 4 [hp_X]/1 mL; CALCIUM SULFIDE 8 [hp_X]/1 mL; HEPATICA NOBILIS VAR. OBTUSA 4 [hp_X]/1 mL; LYCOPODIUM CLAVATUM SPORE 6 [hp_X]/1 mL; PHOSPHORUS 12 [hp_X]/1 mL; TIN 8 [hp_X]/1 mL; LOBARIA PULMONARIA 4 [hp_X]/1 mL
INACTIVE INGREDIENTS: ALCOHOL

Respiratory Complex

Purpose:

Suggested use for one or more of the following symptoms:

Cough,asthma,lung congestion, and bronchial infections.

Usage and Dosage:

For oral use only.

DOSAGE AND ADMINISTRATION

Adults:
In Acute Phase:
12-15 drops, every half hour until relief occurs
When Relief Occurs:
12-15 drops, 4-6 times per day
Children 2-12 years:
8-10 drops, 4-6 times per day

Warnings:

Keep out of reach of children.

WARNINGS

If symptoms persist, consult a physician.
Do not use if ring on bottom of cap is broken or missing.

Active Ingredients:

Antimonium tartaricum 6X, Bryonia 4X, Chelidonium majus 6X, Echinacea angustifolia 4X, Hepar sulphuris calcareum 8X, Hepatica tribola 4X, Lycopodium clavatum 6X, Phosphorus 12X, Stannum metallicum 8X, Sticta pulmonaria 4X

Inactive Ingredients:

Alcohol, 20% USP

QUESTIONS

Manufactured by Nova Homeopathic Therapeutics Inc., Albuquerque, New Mexico USA 87109
1-800-225-8094

PACKAGE LABEL

Respiratory Complex Product

Respiratory Complex Bottle Label

Respiratory Complex Box